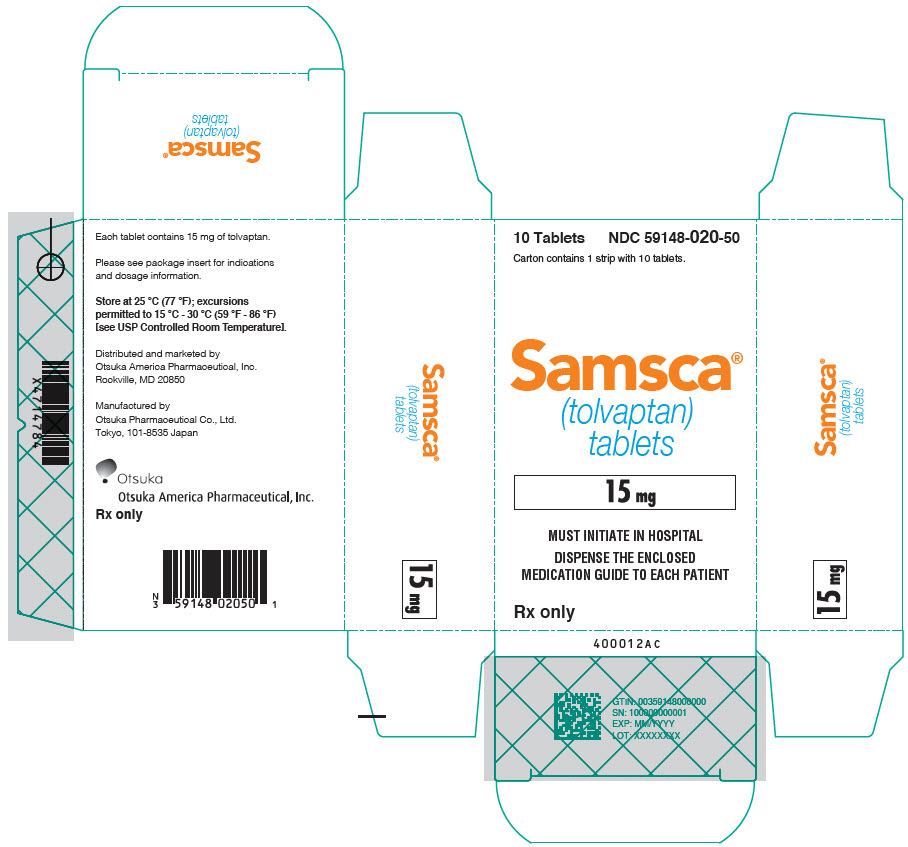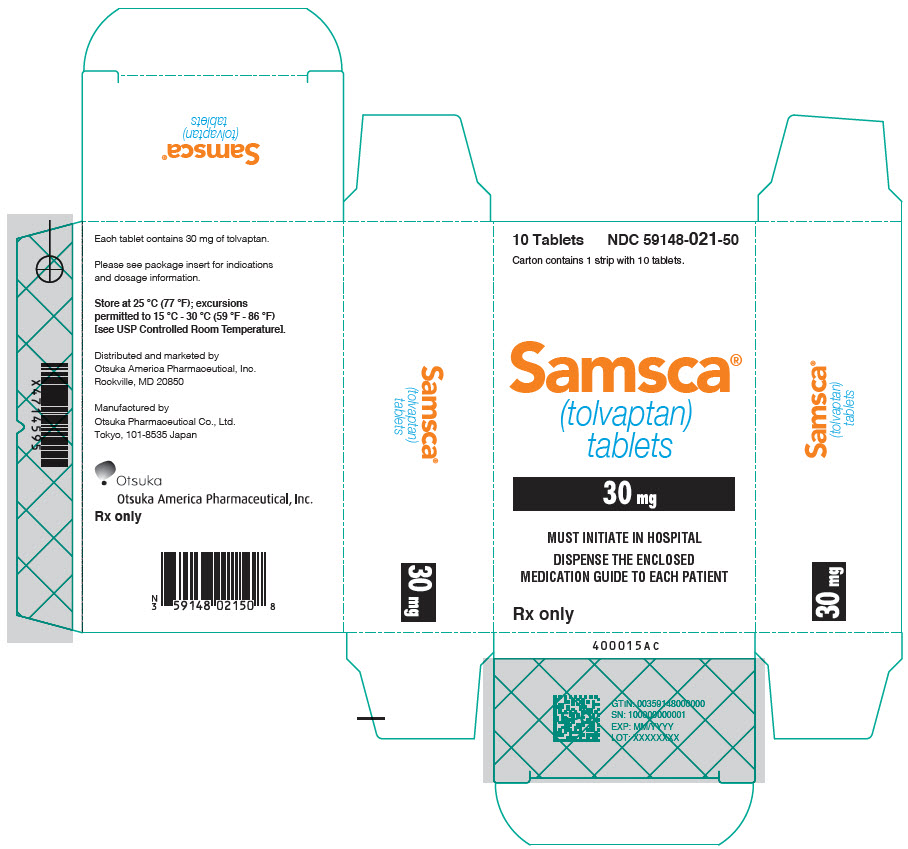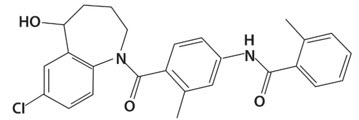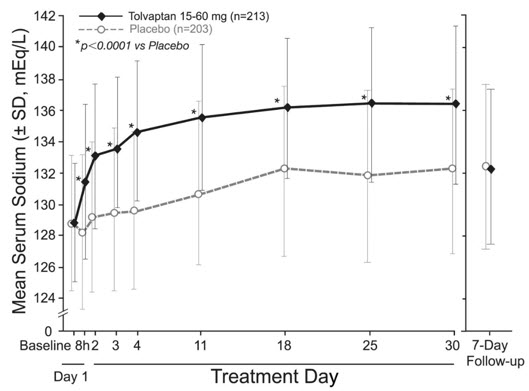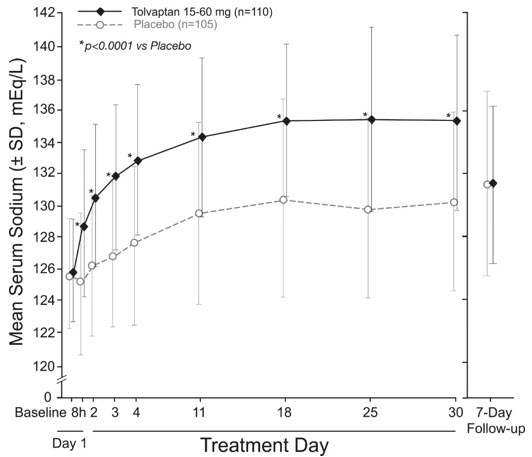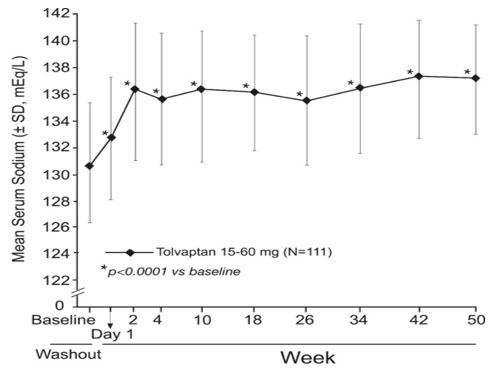 DRUG LABEL: SAMSCA
NDC: 59148-020 | Form: TABLET
Manufacturer: Otsuka America Pharmaceutical, Inc.
Category: prescription | Type: HUMAN PRESCRIPTION DRUG LABEL
Date: 20251114

ACTIVE INGREDIENTS: TOLVAPTAN 15 mg/1 1
INACTIVE INGREDIENTS: STARCH, CORN; HYDROXYPROPYL CELLULOSE, UNSPECIFIED; LACTOSE MONOHYDRATE; LOW-SUBSTITUTED HYDROXYPROPYL CELLULOSE, UNSPECIFIED; MAGNESIUM STEARATE; MICROCRYSTALLINE CELLULOSE; FD&C BLUE NO. 2 ALUMINUM LAKE

HIGHLIGHTS OF PRESCRIBING INFORMATION

These highlights do not include all the information needed to use SAMSCA safely and effectively. See full prescribing information for SAMSCA.
SAMSCA® (tolvaptan) tablets, for oral use
Initial U.S. Approval: 2009

WARNING: (A) INITIATE AND RE-INITIATE IN A HOSPITAL AND MONITOR SERUM SODIUM (B) NOT FOR USE FOR AUTOSOMAL DOMINANT POLYCYSTIC KIDNEY DISEASE (ADPKD)

See full prescribing information for complete boxed warning.

(A) Initiate and re-initiate in a hospital and monitor serum sodium

- SAMSCA should be initiated and re-initiated in patients only in a hospital where serum sodium can be monitored closely.
- Too rapid correction of hyponatremia (e.g., >12 mEq/L/24 hours) can cause osmotic demyelination resulting in dysarthria, mutism, dysphagia, lethargy, affective changes, spastic quadriparesis, seizures, coma and death. In susceptible patients, including those with severe malnutrition, alcoholism or advanced liver disease, slower rates of correction may be advisable.

(B) Not for use for autosomal dominant polycystic kidney disease (ADPKD)

- Because of the risk of hepatotoxicity, tolvaptan should not be used for ADPKD outside of the FDA-approved REMS (4)

RECENT MAJOR CHANGES

Warnings and Precautions (5.5, 5.7) | 04/2021

1 INDICATIONS AND USAGE

SAMSCA is a selective vasopressin V2-receptor antagonist indicated for the treatment of clinically significant hypervolemic and euvolemic hyponatremia [serum sodium <125 mEq/L or less marked hyponatremia that is symptomatic and has resisted correction with fluid restriction], including patients with heart failure and Syndrome of Inappropriate Antidiuretic Hormone (SIADH) (1)

Limitations of Use:

- Patients requiring intervention to raise serum sodium urgently to prevent or to treat serious neurological symptoms should not be treated with SAMSCA (1)
- It has not been established that SAMSCA provides a symptomatic benefit to patients (1)

2 DOSAGE AND ADMINISTRATION

- SAMSCA should be initiated and re-initiated in a hospital (2.1)
- The recommended starting dose is 15 mg once daily. Dosage may be increased at intervals ≥24 hr to 30 mg once daily, and to a maximum of 60 mg once daily as needed to raise serum sodium. (2.1)

3 DOSAGE FORMS AND STRENGTHS

- Tablets: 15 mg and 30 mg (3)

4 CONTRAINDICATIONS

- Use in patients with autosomal dominant polycystic kidney disease (ADPKD) outside of FDA-approved REMS (4)
- Patients who are unable to respond appropriately to thirst (4)
- Hypovolemic hyponatremia (4)
- Concomitant use of strong CYP3A inhibitors (4)
- Anuria (4)
- Hypersensitivity (4)

5 WARNINGS AND PRECAUTIONS

- Liver injury: Limit treatment duration to 30 days. If hepatic injury is suspected, discontinue SAMSCA. Avoid use in patients with underlying liver disease (5.2)
- Dehydration and hypovolemia may require intervention (5.3)
- Avoid use with hypertonic saline (5.4)
- Avoid use with moderate to strong CYP3A inhibitors (5.5)
- Monitor serum potassium in patients with potassium >5 mEq/L or on drugs known to increase potassium (5.6)
- Urinary outflow obstruction: Urinary output must be secured (5.7)

6 ADVERSE REACTIONS

Most common adverse reactions (≥5% placebo) are thirst, dry mouth, asthenia, constipation, pollakiuria or polyuria, and hyperglycemia (6.1)

To report SUSPECTED ADVERSE REACTIONS, contact Otsuka at 1-877-726-7220 or FDA at 1-800-FDA-1088 (www.fda.gov/medwatch).

7 DRUG INTERACTIONS

Avoid concomitant use with:

- Moderate CYP3A inhibitors (7.1)
- Strong CYP3A inducers (7.1)
- V2-receptor antagonists (7.3)

Monitor serum potassium during concomitant therapy with (7.2):

- Angiotensin receptor blockers
- Angiotensin converting enzyme inhibitors
- Potassium sparing diuretics

8 USE IN SPECIFIC POPULATIONS

- Pregnancy: May cause fetal harm (8.1)
- Lactation: Breastfeeding not recommended (8.2)
- Pediatric Use: There are no studies (8.4)

FULL PRESCRIBING INFORMATION

WARNING: (A) INITIATE AND RE-INITIATE IN A HOSPITAL AND MONITOR SERUM SODIUM (B) NOT FOR USE FOR AUTOSOMAL DOMINANT POLYCYSTIC KIDNEY DISEASE (ADPKD)

(A) Initiate and re-initiate in a hospital and monitor serum sodium

SAMSCA should be initiated and re-initiated in patients only in a hospital where serum sodium can be monitored closely.

Too rapid correction of hyponatremia (e.g., >12 mEq/L/24 hours) can cause osmotic demyelination resulting in dysarthria, mutism, dysphagia, lethargy, affective changes, spastic quadriparesis, seizures, coma and death. In susceptible patients, including those with severe malnutrition, alcoholism or advanced liver disease, slower rates of correction may be advisable.

(B) Not for use for autosomal dominant polycystic kidney disease (ADPKD)

Because of the risk of hepatotoxicity, tolvaptan should not be used for ADPKD outside of the FDA-approved REMS [see Contraindications (4)].

1 INDICATIONS AND USAGE

SAMSCA® is indicated for the treatment of clinically significant hypervolemic and euvolemic hyponatremia (serum sodium <125 mEq/L or less marked hyponatremia that is symptomatic and has resisted correction with fluid restriction), including patients with heart failure and Syndrome of Inappropriate Antidiuretic Hormone (SIADH).

Limitations of Use

Patients requiring intervention to raise serum sodium urgently to prevent or to treat serious neurological symptoms should not be treated with SAMSCA.

It has not been established that raising serum sodium with SAMSCA provides a symptomatic benefit to patients.

2 DOSAGE AND ADMINISTRATION

2.1 Recommended Dosage

Patients should be in a hospital for initiation and re-initiation of therapy to evaluate the therapeutic response and because too rapid correction of hyponatremia can cause osmotic demyelination resulting in dysarthria, mutism, dysphagia, lethargy, affective changes, spastic quadriparesis, seizures, coma and death.

The usual starting dose for SAMSCA is 15 mg administered once daily without regard to meals. Increase the dose to 30 mg once daily, after at least 24 hours, to a maximum of 60 mg once daily, as needed to achieve the desired level of serum sodium. Do not administer SAMSCA for more than 30 days to minimize the risk of liver injury [see Warnings and Precautions (5.2)].

During initiation and titration, frequently monitor for changes in serum electrolytes and volume. Avoid fluid restriction during the first 24 hours of therapy. Patients receiving SAMSCA should be advised that they can continue ingestion of fluid in response to thirst [see Warnings and Precautions (5.1)].

2.2 Drug Withdrawal

Following discontinuation from SAMSCA, patients should be advised to resume fluid restriction and should be monitored for changes in serum sodium and volume status.

3 DOSAGE FORMS AND STRENGTHS

SAMSCA is available in the following dosage forms and strengths:

- 15 mg tablets are non-scored, blue, triangular, shallow-convex, debossed with "OTSUKA" and "15" on one side.
- 30 mg tablets are non-scored, blue, round, shallow-convex, debossed with "OTSUKA" and "30" on one side.

4 CONTRAINDICATIONS

SAMSCA is contraindicated in the following conditions:

- Patients with autosomal dominant polycystic kidney disease (ADPKD) outside of FDA-approved REMS [see Warnings and Precautions (5.2)]
- Unable to sense or respond to thirst
- Hypovolemic hyponatremia
- Taking strong CYP3A inhibitors [see Warnings and Precautions (5.5)]
- Anuria
- Hypersensitivity (e.g., anaphylactic shock, rash generalized) to tolvaptan or any components of the product [see Adverse Reactions (6)]

5 WARNINGS AND PRECAUTIONS

5.1 Too Rapid Correction of Serum Sodium Can Cause Serious Neurologic Sequelae

Osmotic demyelination syndrome is a risk associated with too rapid correction of hyponatremia (e.g., >12 mEq/L/24 hours). Osmotic demyelination results in dysarthria, mutism, dysphagia, lethargy, affective changes, spastic quadriparesis, seizures, coma or death. In susceptible patients, including those with severe malnutrition, alcoholism or advanced liver disease, slower rates of correction may be advisable. In controlled clinical trials in which tolvaptan was administered in titrated doses starting at 15 mg once daily, 7% of tolvaptan-treated subjects with a serum sodium <130 mEq/L had an increase in serum sodium greater than 8 mEq/L at approximately 8 hours and 2% had an increase greater than 12 mEq/L at 24 hours. Approximately 1% of placebo-treated subjects with a serum sodium <130 mEq/L had a rise greater than 8 mEq/L at 8 hours and no patient had a rise greater than 12 mEq/L/24 hours. Osmotic demyelination syndrome has been reported in association with SAMSCA therapy [see Adverse Reactions (6.2)]. Patients treated with SAMSCA should be monitored to assess serum sodium concentrations and neurologic status, especially during initiation and after titration. Subjects with SIADH or very low baseline serum sodium concentrations may be at greater risk for too-rapid correction of serum sodium. In patients receiving SAMSCA who develop too rapid a rise in serum sodium, discontinue or interrupt treatment with SAMSCA and consider administration of hypotonic fluid. Fluid restriction during the first 24 hours of therapy with SAMSCA may increase the likelihood of overly rapid correction of serum sodium and should generally be avoided. Co-administration of diuretics also increases the risk of too rapid correction of serum sodium and such patients should undergo close monitoring of serum sodium.

5.2 Liver Injury

Tolvaptan can cause serious and potentially fatal liver injury. In placebo-controlled studies and an open-label extension study of chronically administered tolvaptan in patients with ADPKD, cases of serious liver injury attributed to tolvaptan, generally occurring during the first 18 months of therapy, were observed. In postmarketing experience with tolvaptan in ADPKD, acute injury resulting in liver failure requiring liver transplantation has been reported. Tolvaptan should not be used to treat ADPKD outside of the FDA-approved risk evaluation and mitigation strategy (REMS) for ADPKD patients [see Contraindications (4)].

Patients with symptoms that may indicate liver injury, including fatigue, anorexia, right upper abdominal discomfort, dark urine or jaundice should discontinue treatment with SAMSCA.

Limit duration of therapy with SAMSCA to 30 days. Avoid use in patients with underlying liver disease, including cirrhosis, because the ability to recover from liver injury may be impaired [see Adverse Reactions (6.1)].

5.3 Dehydration and Hypovolemia

SAMSCA therapy induces copious aquaresis, which is normally partially offset by fluid intake. Dehydration and hypovolemia can occur, especially in potentially volume-depleted patients receiving diuretics or those who are fluid restricted. In multiple-dose, placebo-controlled trials in which 607 hyponatremic patients were treated with tolvaptan, the incidence of dehydration was 3.3% for tolvaptan and 1.5% for placebo-treated patients. In patients receiving SAMSCA who develop medically significant signs or symptoms of hypovolemia, interrupt or discontinue SAMSCA therapy and provide supportive care with careful management of vital signs, fluid balance and electrolytes. Fluid restriction during therapy with SAMSCA may increase the risk of dehydration and hypovolemia. Patients receiving SAMSCA should continue ingestion of fluid in response to thirst.

5.4 Co-administration with Hypertonic Saline

Concomitant use with hypertonic saline is not recommended.

5.5 Drug Interactions

Tolvaptan is a substrate of CYP3A. Moderate to strong CYP3A inhibitors can lead to a marked increase in tolvaptan concentrations [see Drug Interactions (7.1)]. Do not use SAMSCA with strong inhibitors of CYP3A [see Contraindications (4)] and avoid concomitant use with moderate CYP3A inhibitors.

5.6 Hyperkalemia or Drugs that Increase Serum Potassium

Treatment with tolvaptan is associated with an acute reduction of the extracellular fluid volume which could result in increased serum potassium. Serum potassium levels should be monitored after initiation of tolvaptan treatment in patients with a serum potassium >5 mEq/L as well as those who are receiving drugs known to increase serum potassium levels.

5.7 Acute Urinary Retention with Outflow Obstruction

Patients with partial obstruction of urinary outflow, for example, patients with prostatic hypertrophy or impairment of micturition, have an increased risk of developing acute retention. Do not administer tolvaptan in patients with uncorrected urinary outflow obstruction.

6 ADVERSE REACTIONS

6.1 Clinical Trials Experience

Because clinical trials are conducted under widely varying conditions, adverse reactions rates observed in the clinical trials of a drug cannot be directly compared to rates in the clinical trials of another drug and may not reflect the rates observed in practice. The adverse event information from clinical trials does, however, provide a basis for identifying the adverse events that appear to be related to drug use and for approximating rates.

In multiple-dose, placebo-controlled trials, 607 hyponatremic patients (serum sodium <135 mEq/L) were treated with SAMSCA. The mean age of these patients was 62 years; 70% of patients were male and 82% were Caucasian. One hundred eighty-nine (189) tolvaptan-treated patients had a serum sodium <130 mEq/L, and 52 patients had a serum sodium <125 mEq/L. Hyponatremia was attributed to cirrhosis in 17% of patients, heart failure in 68% and SIADH/other in 16%. Of these patients, 223 were treated with the recommended dose titration (15 mg titrated to 60 mg as needed to raise serum sodium).

Overall, over 4,000 patients have been treated with oral doses of tolvaptan in open-label or placebo-controlled clinical trials. Approximately 650 of these patients had hyponatremia; approximately 219 of these hyponatremic patients were treated with tolvaptan for 6 months or more.

The most common adverse reactions (incidence ≥5% more than placebo) seen in two 30‑day, double-blind, placebo-controlled hyponatremia trials in which tolvaptan was administered in titrated doses (15 mg to 60 mg once daily) were thirst, dry mouth, asthenia, constipation, pollakiuria or polyuria and hyperglycemia. In these trials, 10% (23/223) of tolvaptan-treated patients discontinued treatment because of an adverse event, compared to 12% (26/220) of placebo-treated patients; no adverse reaction resulting in discontinuation of trial medication occurred at an incidence of >1% in tolvaptan-treated patients.

Table 1 lists the adverse reactions reported in tolvaptan-treated patients with hyponatremia (serum sodium <135 mEq/L) and at a rate at least 2% greater than placebo-treated patients in two 30‑day, double-blind, placebo-controlled trials. In these studies, 223 patients were exposed to tolvaptan (starting dose 15 mg, titrated to 30 and 60 mg as needed to raise serum sodium). Adverse events resulting in death in these trials were 6% in tolvaptan-treated patients and 6% in placebo-treated patients.

Table 1. Adverse Reactions (>2% more than placebo) in Tolvaptan-Treated Patients in Double-Blind, Placebo-Controlled Hyponatremia Trials
System Organ Class MedDRA Preferred Term | Tolvaptan 15 mg/day to 60 mg/day (N =223) n (%) | Placebo (N =220) n (%)
Gastrointestinal Disorders
Dry mouth | 28 (13) | 9 (4)
Constipation | 16 (7) | 4 (2)
General Disorders and Administration Site Conditions
Thirst [polydipsia,] | 35 (16) | 11 (5)
Asthenia | 19 (9) | 9 (4)
Pyrexia | 9 (4) | 2 (1)
Metabolism and Nutrition Disorders
Hyperglycemia [diabetes mellitus,] | 14 (6) | 2 (1)
Anorexia [decreased appetite,] | 8 (4) | 2 (1)
Renal and Urinary Disorders
Pollakiuria or polyuria [urine output increased, micturition urgency, nocturia] | 25 (11) | 7 (3)
The following terms are subsumed under the referenced ADR in Table 1:

In a subgroup of patients with hyponatremia (N =475, serum sodium <135 mEq/L) enrolled in a double-blind, placebo-controlled trial (mean duration of treatment was 9 months) of patients with worsening heart failure, the following adverse reactions occurred in tolvaptan-treated patients at a rate at least 2% greater than placebo: mortality (42% tolvaptan, 38% placebo), nausea (21% tolvaptan, 16% placebo), thirst (12% tolvaptan, 2% placebo), dry mouth (7% tolvaptan, 2% placebo) and polyuria or pollakiuria (4% tolvaptan, 1% placebo).

Gastrointestinal bleeding in patients with cirrhosis

In patients with cirrhosis treated with tolvaptan in the hyponatremia trials, gastrointestinal bleeding was reported in 6 out of 63 (10%) tolvaptan-treated patients and 1 out of 57 (2%) placebo treated patients.

The following adverse reactions occurred in <2% of hyponatremic patients treated with SAMSCA and at a rate greater than placebo in double-blind placebo-controlled trials (N =607 tolvaptan; N =518 placebo) or in <2% of patients in an uncontrolled trial of patients with hyponatremia (N =111) and are not mentioned elsewhere in the label.

Blood and Lymphatic System Disorders: Disseminated intravascular coagulation

Cardiac Disorders: Intracardiac thrombus, ventricular fibrillation

Investigations: Prothrombin time prolonged

Gastrointestinal Disorders: Ischemic colitis

Metabolism and Nutrition Disorders: Diabetic ketoacidosis

Musculoskeletal and Connective Tissue Disorders: Rhabdomyolysis

Nervous System: Cerebrovascular accident

Renal and Urinary Disorders: Urethral hemorrhage

Reproductive System and Breast Disorders (female): Vaginal hemorrhage

Respiratory, Thoracic, and Mediastinal Disorders: Pulmonary embolism, respiratory failure

Vascular disorder: Deep vein thrombosis

6.2 Postmarketing Experience

The following adverse reactions have been identified during post-approval use of SAMSCA. Because these reactions are reported voluntarily from a population of an unknown size, it is not always possible to reliably estimate their frequency or establish a causal relationship to drug exposure.

Neurologic: Osmotic demyelination syndrome

Investigations: Hypernatremia

Removal of excess free body water increases serum osmolality and serum sodium concentrations. All patients treated with tolvaptan, especially those whose serum sodium levels become normal, should continue to be monitored to ensure serum sodium remains within normal limits. If hypernatremia is observed, management may include dose decreases or interruption of tolvaptan treatment, combined with modification of free-water intake or infusion. During clinical trials of hyponatremic patients, hypernatremia was reported as an adverse event in 0.7% of patients receiving tolvaptan vs. 0.6% of patients receiving placebo; analysis of laboratory values demonstrated an incidence of hypernatremia of 1.7% in patients receiving tolvaptan vs. 0.8% in patients receiving placebo.

Immune System Disorders: Hypersensitivity reactions including anaphylactic shock and rash generalized.

7 DRUG INTERACTIONS

7.1 CYP3A Inhibitors and Inducers

Strong CYP3A Inhibitors

Tolvaptan's AUC was 5.4 times as large and Cmax was 3.5 times as large after co-administration of tolvaptan and 200 mg ketoconazole [see Warnings and Precautions (5.5) and Clinical Pharmacology (12.3)]. Larger doses of the strong CYP3A inhibitor would be expected to produce larger increases in tolvaptan exposure. Concomitant use of tolvaptan with strong CYP3A inhibitors is contraindicated [see Contraindications (4)].

Moderate CYP3A Inhibitors

A substantial increase in the exposure to tolvaptan would be expected when SAMSCA is co-administered with moderate CYP3A inhibitors. Avoid co-administration of SAMSCA with moderate CYP3A inhibitors [see Warnings and Precautions (5.5)].

Patients should avoid grapefruit juice beverages while taking SAMSCA [see Clinical Pharmacology (12.3)].

Strong CYP3A Inducers

Co-administration of SAMSCA with strong CYP3A inducers reduces exposure to SAMSCA [see Clinical Pharmacology (12.3)]. Avoid concomitant use of SAMSCA with strong CYP3A inducers.

7.2 Angiotensin Receptor Blockers, Angiotensin Converting Enzyme Inhibitors and Potassium Sparing Diuretics

Although specific interaction studies were not performed, in clinical studies, tolvaptan was used concomitantly with beta-blockers, angiotensin receptor blockers, angiotensin converting enzyme inhibitors and potassium sparing diuretics. Adverse reactions of hyperkalemia were approximately 1 to 2% higher when tolvaptan was administered with angiotensin receptor blockers, angiotensin converting enzyme inhibitors and potassium sparing diuretics compared to administration of these medications with placebo. Serum potassium levels should be monitored during concomitant drug therapy.

7.3 V2-Receptor Agonist

As a V2-receptor antagonist, tolvaptan may interfere with the V2-agonist activity of desmopressin (dDAVP). Avoid concomitant use of SAMSCA with a V2-agonist.

8 USE IN SPECIFIC POPULATIONS

8.1 Pregnancy

Risk Summary

Available data with SAMSCA use in pregnant women are insufficient to determine if there is a drug-associated risk of adverse developmental outcomes. Tolvaptan did not cause any developmental toxicity in rats or in rabbits at exposures approximately 2.8 and 0.8 times, respectively, the exposure in congestive heart failure (CHF) patients at the maximum recommended human dose (MRHD) of 60 mg once daily. However, effects on embryo-fetal development occurred in both species at doses causing significant maternally toxic doses. In rats, reduced fetal weights and delayed fetal ossification occurred at 11 times the exposure in CHF patients, based on AUC. In rabbits, increased abortions, embryo-fetal death, fetal microphthalmia, open eyelids, cleft palate, brachymelia and skeletal malformations occurred at approximately 1.6 times the exposure in CHF patients (see Data).

The estimated background risk of major birth defects and miscarriage for the indicated population is unknown. All pregnancies have a background risk of birth defect, loss, or other adverse outcomes. The estimated background risk of major birth defects and miscarriage in the U.S. general population is 2 to 4% and 15 to 20% of clinically recognized pregnancies, respectively.

Data

Animal Data

Oral administration of tolvaptan during the period of organogenesis in Sprague-Dawley rats produced no evidence of teratogenesis at doses up to 100 mg/kg/day. Delayed ossification was seen at 1000 mg/kg, which is approximately 11 times the exposure in CHF patients at the MRHD of 60 mg (AUC24h 10271 ng*h/mL). The fetal effects are likely secondary to maternal toxicity (decreased food intake and low body weights). In a prenatal and postnatal study in rats, tolvaptan had no effect on physical development, reflex function, learning ability or reproductive performance at doses up to 1000 mg/kg/day (11 times the exposure in CHF patients at the MRHD of 60 mg).

In rabbits, teratogenicity (microphthalmia, embryo-fetal mortality, cleft palate, brachymelia and skeletal malformations) was observed in rabbits at 1000 mg/kg (approximately 1.6 times the exposure in CHF patients at the MRHD of 60 mg dose). This dose also caused maternal toxicity (lower body weight gains and food consumption).

8.2 Lactation

Risk Summary

There are no data on the presence of tolvaptan or its metabolites in human milk, the effects on the breastfed infant, or the effects on milk production. Tolvaptan is present in rat milk (see Data). When a drug is present in animal milk, it is possible that the drug will be present in human milk, but relative levels may vary (see Data). Because of the potential for serious adverse reactions, including electrolyte abnormalities (e.g., hypernatremia), hypotension, and volume depletion in breastfed infants, advise women not to breastfeed during treatment with SAMSCA.

Data

In lactating rats administered radiolabeled tolvaptan, lacteal radioactivity concentrations reached the highest level at 8 hours after administration and then decreased gradually with time with a half-life of 27.3 hours. The level of activity in milk ranged from 1.5- to 15.8-fold those in maternal blood over a period of 72 hours post-dose. Increased perinatal death and decreased body weight of the offspring were observed during the lactation period and after weaning at approximately 11 times the exposure in CHF patients at the MRHD of 60 mg.

8.4 Pediatric Use

Safety and effectiveness of SAMSCA in pediatric patients have not been established.

8.5 Geriatric Use

Of the total number of hyponatremic subjects treated with SAMSCA in clinical studies, 42% were 65 years old and over, while 19% were 75 years old and over. No overall differences in safety or effectiveness were observed between these subjects and younger subjects, and other reported clinical experience has not identified differences in responses between the elderly and younger patients, but greater sensitivity of some older individuals cannot be ruled out. Increasing age has no effect on tolvaptan plasma concentrations.

8.6 Use in Patients with Hepatic Impairment

Moderate and severe hepatic impairment do not affect exposure to tolvaptan to a clinically relevant extent. Avoid use of tolvaptan in patients with underlying liver disease.

8.7 Use in Patients with Renal Impairment

No dose adjustment is necessary based on renal function. There are no clinical trial data in patients with CrCl <10 mL/min, and, because drug effects on serum sodium levels are likely lost at very low levels of renal function, use in patients with a CrCl <10 mL/min is not recommended. No benefit can be expected in patients who are anuric [see Contraindications (4) and Clinical Pharmacology (12.3)].

10 OVERDOSAGE

Single oral doses up to 480 mg (8 times the maximum recommended daily dose) and multiple doses up to 300 mg once daily for 5 days have been well tolerated in studies in healthy subjects. There is no specific antidote for tolvaptan intoxication. The signs and symptoms of an acute overdose can be anticipated to be those of excessive pharmacologic effect: a rise in serum sodium concentration, polyuria, thirst, and dehydration/hypovolemia.

No mortality was observed in rats or dogs following single oral doses of 2000 mg/kg (maximum feasible dose). A single oral dose of 2000 mg/kg was lethal in mice, and symptoms of toxicity in affected mice included decreased locomotor activity, staggering gait, tremor and hypothermia.

In patients with suspected SAMSCA overdosage, assessment of vital signs, electrolyte concentrations, ECG and fluid status are recommended. Continue replacement of water and electrolytes until aquaresis abates.

Dialysis may not be effective in removing tolvaptan because of its high binding affinity for human plasma protein (>98%).

11 DESCRIPTION

SAMSCA contains tolvaptan, a selective vasopressin V2-receptor antagonist in tablets for oral use available in 15 mg or 30 mg strengths. Tolvaptan is (±)-4'-[(7-chloro-2,3,4,5-tetrahydro-5-hydroxy-1H-1-benzazepin-1-yl) carbonyl]-o-tolu-m-toluidide. The empirical formula is C26H25ClN2O3. Molecular weight is 448.94. The chemical structure is:

Inactive ingredients include corn starch, hydroxypropyl cellulose, lactose monohydrate, low-substituted hydroxypropyl cellulose, magnesium stearate, microcrystalline cellulose, and FD&C Blue No. 2 Aluminum Lake as colorant.

12 CLINICAL PHARMACOLOGY

12.1 Mechanism of Action

Tolvaptan is a selective vasopressin V2-receptor antagonist with an affinity for the V2-receptor that is 1.8 times that of native arginine vasopressin (AVP). Tolvaptan affinity for the V2-receptor is 29 times greater than for the V1a-receptor. When taken orally, 15 to 60 mg doses of tolvaptan antagonize the effect of vasopressin and cause an increase in urine water excretion that results in an increase in free water clearance (aquaresis), a decrease in urine osmolality, and a resulting increase in serum sodium concentrations. Urinary excretion of sodium and potassium and plasma potassium concentrations are not significantly changed. Tolvaptan metabolites have no or weak antagonist activity for human V2-receptors compared with tolvaptan.

12.2 Pharmacodynamics

In healthy subjects receiving a single dose of SAMSCA 60 mg, the onset of the aquaretic and sodium increasing effects occurs within 2 to 4 hours post-dose. A peak effect of about a 6 mEq increase in serum sodium and about 9 mL/min increase in urine excretion rate is observed between 4 and 8 hours post-dose; thus, the pharmacological activity lags behind the plasma concentrations of tolvaptan. About 60% of the peak effect on serum sodium is sustained at 24 hours post-dose, but the urinary excretion rate is no longer elevated by this time. Doses above 60 mg tolvaptan do not increase aquaresis or serum sodium further. The effects of tolvaptan in the recommended dose range of 15 to 60 mg once daily appear to be limited to aquaresis and the resulting increase in sodium concentration.

Plasma concentrations of native AVP may increase (avg. 2 to 9 pg/mL) with tolvaptan administration.

Cardiac Electrophysiology

No prolongation of the QT interval was observed with tolvaptan following multiple doses of 300 mg/day for 5 days.

12.3 Pharmacokinetics

In healthy subjects, the pharmacokinetics of tolvaptan after single doses of up to 480 mg and multiple doses up to 300 mg once daily have been examined. In hyponatremia subjects, single and multiple doses up to 60 mg have been studied.

Absorption

In healthy subjects, peak concentrations of tolvaptan are observed between 2 and 4 hours post-dose. Peak concentrations increase less than dose proportionally with doses greater than 240 mg.

The absolute bioavailability of tolvaptan decreases with increasing doses. The absolute bioavailability of tolvaptan following an oral dose of 30 mg is 56% (range 42 to 80%).

Co-administration of 90 mg tolvaptan with a high-fat meal (~1000 calories, of which 50% are from fat) doubles peak concentrations but has no effect on the AUC of tolvaptan; tolvaptan may be administered with or without food.

Distribution

Tolvaptan binds to both albumin and α1-acid glycoprotein and the overall protein binding is >98%; binding is not affected by disease state. The volume of distribution of tolvaptan is about 3 L/kg. The pharmacokinetic properties of tolvaptan are stereospecific, with a steady-state ratio of the S-(-) to the R-(+) enantiomer of about 3. When administered as multiple once-daily 300 mg doses to healthy subjects or to patients with congestive heart failure or ADPKD, tolvaptan's accumulation factor is <1.2. There is marked inter-subject variation in peak and average exposure to tolvaptan with a percent coefficient of variation ranging between 30 and 60%.

Metabolism and Elimination

Tolvaptan is metabolized almost exclusively by CYP3A. Fourteen metabolites have been identified in plasma, urine and feces; all but one were also metabolized by CYP3A and none are pharmacodynamically active. After oral administration of radiolabeled tolvaptan, tolvaptan was a minor component in plasma, representing 3% of total plasma radioactivity; the oxobutyric acid metabolite was present at 52.5% of total plasma radioactivity with all other metabolites present at lower concentrations than tolvaptan. The oxobutyric acid metabolite shows a plasma half-life of ~180 h. About 40% of radioactivity was recovered in urine (<1% as unchanged tolvaptan) and 59% in feces (19% as unchanged tolvaptan). Following intravenous infusion, tolvaptan half-life is approximately 3 hours. Following single oral doses to healthy subjects, the estimated half-life of tolvaptan increases from 3 hours for a 15 mg dose to approximately 12 hours for 120 mg and higher doses due to more prolonged absorption of tolvaptan at higher doses; apparent clearance is approximately 4 mL/min/kg and does not appear to change with increasing dose.

Specific Populations

Hyponatremia

In patients with hyponatremia of any origin the clearance of tolvaptan is reduced to about 2 mL/min/kg.

Hepatic Impairment

Moderate or severe hepatic impairment or congestive heart failure decrease the clearance and increase the volume of distribution of tolvaptan, but the respective changes are not clinically relevant. Exposure and response to tolvaptan in subjects with creatinine clearance ranging between 79 and 10 mL/min and patients with normal renal function are not different.

Renal Impairment

In a study in patients with creatinine clearances ranging from 10 to 124 mL/min administered a single dose of 60 mg tolvaptan, AUC and Cmax of plasma tolvaptan were less than doubled in patients with severe renal impairment (creatinine clearance <30 mL/min) relative to the controls. The peak increase in serum sodium was 5 to 6 mEq/L, regardless of renal function, but the onset and offset of tolvaptan's effect on serum sodium were slower in patients with severe renal impairment [see Use in Specific Populations (8.7)].

Drug Interaction Studies

Impact of Other Drugs on Tolvaptan

Strong CYP3A Inhibitors

Ketoconazole: Tolvaptan's Cmax and AUC were, respectively, 3.5 times and 5.4 times as high following ketoconazole 200 mg given one day prior to and concomitantly with 30 mg tolvaptan [see Contraindications (4), Warnings and Precautions (5.5) and Drug Interactions (7.1)].

Moderate CYP3A4 inhibitors

Fluconazole: Fluconazole 400 mg given one day prior and 200 mg given concomitantly produced an 80% and 200% increase in tolvaptan Cmax and AUC, respectively.

Grapefruit Juice: Co-administration of grapefruit juice and tolvaptan results in an increase in Cmax and AUC of 90% and 60% for tolvaptan, respectively [see Drug Interactions (7.1)].

CYP3A4 Inducers

Rifampin: Rifampin 600 mg once daily for 7 days followed by a single 240 mg dose of tolvaptan decreased both tolvaptan Cmax and AUC about 85%.

Other Drugs

Co-administration of lovastatin, digoxin, furosemide, and hydrochlorothiazide with SAMSCA has no clinically relevant impact on the exposure to tolvaptan.

Impact of Tolvaptan on Other Drugs

CYP3A Substrates

SAMSCA is a weak inhibitor of CYP3A. Co-administration of lovastatin and SAMSCA increases the exposure to lovastatin and its active metabolite lovastatin-β hydroxyacid by factors of 1.4 and 1.3, respectively. This is not a clinically relevant change.

P-gp Substrates

Digoxin: Digoxin 0.25 mg was administered once daily for 12 days. Tolvaptan 60 mg, was co-administered once daily on Days 8 to 12. Digoxin Cmax and AUC were increased 30% and 20%, respectively.

Transporter Substrates

Tolvaptan is a substrate of P-gp and an inhibitor of P-gp and BCRP. The oxobutyric acid metabolite of tolvaptan is an inhibitor of OATP1B1 and OAT3. Co-administration of tolvaptan with rosuvastatin (BCRP substrate) did not have a clinically significant effect on rosuvastatin exposure. Rosuvastatin Cmax and AUCt increased 54% and 69%, respectively. Administration of rosuvastatin (OATP1B1 substrate) or furosemide (OAT3 substrate) to healthy subjects with elevated oxobutyric acid metabolite plasma concentrations did not meaningfully alter the pharmacokinetics of rosuvastatin or furosemide.

Other Drugs

Co-administration of tolvaptan does not appear to alter the pharmacokinetics of warfarin, furosemide, hydrochlorothiazide, or amiodarone (or its active metabolite, desethylamiodarone) to a clinically significant degree.

13 NONCLINICAL TOXICOLOGY

13.1 Carcinogenesis, Mutagenesis, Impairment of Fertility

Carcinogenesis

The carcinogenic potential of tolvaptan was assessed in 2-year carcinogenicity studies in mice and rats. Tolvaptan did not increase tumors in male or female rats at doses up to 1000 mg/kg/day (1.24 to 3.26 times the exposure in CHF patients based on AUC at the MRHD of 60 mg), in male mice at doses up to 60 mg/kg/day (0.3 times the exposure in CHF patients at the MRHD) and to female mice at doses up to 100 mg/kg/day (0.4 times the exposure in CHF patients at the MRHD).

Mutagenesis

Tolvaptan was not clastogenic in the in vitro chromosomal aberration test in Chinese hamster lung fibroblast cells or the in vivo rat micronucleus assay and was not mutagenic in the in vitro bacterial reverse mutation assays.

Impairment of fertility

In a fertility study in which male and female rats were administered tolvaptan orally at 100, 300 or 1000 mg/kg/day, altered estrous cycles due to prolongation of diestrus were observed in dams given 300 and 1000 mg/kg/day (6.2 and 11 times the exposure in CHF patients at the 60 mg dose). Tolvaptan had no effect on copulation or fertility indices. There were also no effects on the incidences of early or late resorption, dead fetuses, pre- or post-implantation loss, external anomalies, or fetal body weights.

14 CLINICAL STUDIES

14.1 Hyponatremia

In two double-blind, placebo-controlled, multi-center studies (SALT-1 and SALT-2), a total of 424 patients with euvolemic or hypervolemic hyponatremia (serum sodium <135 mEq/L) resulting from a variety of underlying causes (heart failure, liver cirrhosis, syndrome of inappropriate antidiuretic hormone [SIADH] and others) were treated for 30 days with tolvaptan or placebo, then followed for an additional 7 days after withdrawal. Symptomatic patients, patients likely to require saline therapy during the course of therapy, patients with acute and transient hyponatremia associated with head trauma or postoperative state and patients with hyponatremia due to primary polydipsia, uncontrolled adrenal insufficiency or uncontrolled hypothyroidism were excluded. Patients were randomized to receive either placebo (N =220) or tolvaptan (N =223) at an initial oral dose of 15 mg once daily. The mean serum sodium concentration at study entry was 129 mEq/L. Fluid restriction was to be avoided if possible during the first 24 hours of therapy to avoid overly rapid correction of serum sodium, and during the first 24 hours of therapy 87% of patients had no fluid restriction. Thereafter, patients could resume or initiate fluid restriction (defined as daily fluid intake of ≤1.0 liter/day) as clinically indicated.

The dose of tolvaptan could be increased at 24-hour intervals to 30 mg once daily, then to 60 mg once daily, until either the maximum dose of 60 mg or normonatremia (serum sodium >135 mEq/L) was reached. Serum sodium concentrations were determined at 8 hours after study drug initiation and daily up to 72 hours, within which time titration was typically completed. Treatment was maintained for 30 days with additional serum sodium assessments on Days 11, 18, 25 and 30. On the day of study discontinuation, all patients resumed previous therapies for hyponatremia and were reevaluated 7 days later. The primary endpoint for these studies was the average daily AUC for change in serum sodium from baseline to Day 4 and baseline to Day 30 in patients with a serum sodium less than 135 mEq/L. Compared to placebo, tolvaptan caused a statistically greater increase in serum sodium (p <0.0001) during both periods in both studies (see Table 2). For patients with a serum sodium of <130 mEq/L or <125 mEq/L, the effects at Day 4 and Day 30 remained significant (see Table 2). This effect was also seen across all disease etiology subsets (e.g., CHF, cirrhosis, SIADH/other).

Table 2. Effects of Treatment with Tolvaptan 15 mg/day to 60 mg/day
 | Tolvaptan 15 mg/day to 60 mg/day | Placebo | Estimated Effect (95% CI)
Subjects with Serum Sodium <135 mEq/L (ITT population)
Change in average daily serum [Na+] AUC baseline to Day 4 (mEq/L) Mean (SD) N | 4.0 (2.8) 213 | 0.4 (2.4) 203 | 3.7 (3.3 to 4.2) p <0.0001
Change in average daily serum [Na+] AUC baseline to Day 30 (mEq/L) Mean (SD) N | 6.2 (4.0) 213 | 1.8 (3.7) 203 | 4.6 (3.9 to 5.2) p <0.0001
Percent of Patients Needing Fluid Restriction [Fluid Restriction defined as <1L/day at any time during treatment period.] | 14% 30/215 | 25% 51/206 | p =0.0017
Subgroup with Serum Sodium <130 mEq/L
Change in average daily serum [Na+] AUC baseline to Day 4 (mEq/L) Mean (SD) N | 4.8 (3.0) 110 | 0.7 (2.5) 105 | 4.2 (3.5 to 5.0) p <0.0001
Change in average daily serum [Na+] AUC baseline to Day 30 (mEq/L) Mean (SD) N | 7.9 (4.1) 110 | 2.6 (4.2) 105 | 5.5 (4.4 to 6.5) p <0.0001
Percent of Patients Needing Fluid Restriction | 19% 21/110 | 36% 38/106 | p <0.01
Subgroup with Serum Sodium <125 mEq/L
Change in average daily serum [Na+] AUC baseline to Day 4 (mEq/L) Mean (SD) N | 5.7 (3.8) 26 | 1.0 (1.8) 30 | 5.3 (3.8 to 6.9) p <0.0001
Change in average daily serum [Na+] AUC baseline to Day 30 (mEq/L) Mean (SD) N | 10.0 (4.8) 26 | 4.1 (4.5) 30 | 5.7 (3.1 to 8.3) p <0.0001
Percent of Patients Needing Fluid Restriction | 35% 9/26 | 50% 15/30 | p =0.14

In patients with hyponatremia (defined as <135 mEq/L), serum sodium concentration increased to a significantly greater degree in tolvaptan-treated patients compared to placebo-treated patients as early as 8 hours after the first dose, and the change was maintained for 30 days. The percentage of patients requiring fluid restriction (defined as ≤1 L/day at any time during the treatment period) was also significantly less (p =0.0017) in the tolvaptan-treated group (30/215, 14%) as compared with the placebo-treated group (51/206, 25%).

Figure 1 shows the change from baseline in serum sodium by visit in patients with serum sodium <135 mEq/L. Within 7 days of tolvaptan discontinuation, serum sodium concentrations in tolvaptan-treated patients declined to levels similar to those of placebo-treated patients.

Figure 1: Pooled SALT Studies: Analysis of Mean Serum Sodium (± SD, mEq/L) by Visit - Patients with Baseline Serum Sodium <135 mEq/L

*p-value <0.0001 for all visits during tolvaptan treatment compared to placebo

Figure 2: Pooled SALT Studies: Analysis of Mean Serum Sodium (± SD, mEq/L) by Visit - Patients with Baseline Serum Sodium <130 mEq/L

*p-value <0.0001 for all visits during tolvaptan treatment compared to placebo

In the open-label study SALTWATER, 111 patients, 94 of them hyponatremic (serum sodium <135 mEq/L), previously on tolvaptan or placebo therapy, were given tolvaptan as a titrated regimen (15 to 60 mg once daily) after having returned to standard care for at least 7 days. By this time, their baseline mean serum sodium concentration had fallen to between their original baseline and post-placebo therapy level. Upon initiation of therapy, average serum sodium concentrations increased to approximately the same levels as observed for those previously treated with tolvaptan and were sustained for at least a year. Figure 3 shows results from 111 patients enrolled in the SALTWATER Study.

Figure 3: SALTWATER: Analysis of Mean Serum Sodium (± SD, mEq/L) by Visit

*p-value <0.0001 for all visits during tolvaptan treatment compared to baseline

14.2 Heart Failure

In a phase 3 double-blind, placebo-controlled study (EVEREST), 4133 patients with worsening heart failure were randomized to tolvaptan or placebo as an adjunct to standard of care. Long-term tolvaptan treatment (mean duration of treatment of 0.75 years) had no demonstrated effect, either favorable or unfavorable, on all-cause mortality [HR (95% CI): 0.98 (0.9, 1.1)] or the combined endpoint of CV mortality or subsequent hospitalization for worsening HF [HR (95% CI): 1.0 (0.9, 1.1)].

16 HOW SUPPLIED/STORAGE AND HANDLING

How Supplied

SAMSCA® (tolvaptan) tablets are available in the following strengths and packages.

SAMSCA 15 mg tablets are non-scored, blue, triangular, shallow-convex, debossed with "OTSUKA" and "15" on one side.

Blister of 10 | NDC 59148-020-50

SAMSCA 30 mg tablets are non-scored, blue, round, shallow-convex, debossed with "OTSUKA" and "30" on one side.

Blister of 10 | NDC 59148-021-50

Storage and Handling

Store at 25°C (77°F), excursions permitted between 15°C and 30°C (59°F to 86°F) [see USP controlled Room Temperature].

Keep out of reach of children.

17 PATIENT COUNSELING INFORMATION

As a part of patient counseling, healthcare providers must review the SAMSCA Medication Guide with every patient [see FDA-Approved Medication Guide].

Pregnancy

Advise pregnant women of the potential risk to a fetus. Advise females of reproductive potential to inform their prescriber of a known or suspected pregnancy [see Use in Specific Populations (8.1)].

Lactation

Advise patients not to breastfeed an infant if they are taking SAMSCA [see Use in Specific Populations (8.2)].

Manufactured by Otsuka Pharmaceutical Co., Ltd., Tokyo, 101-8535 Japan

Distributed and marketed by Otsuka America Pharmaceutical, Inc., Rockville, MD 20850

SAMSCA is a registered trademark of Otsuka Pharmaceutical Co., Ltd., Tokyo, 101-8535 Japan

©2021 Otsuka Pharmaceutical Co., Ltd.

MEDICATION GUIDE

SAMSCA® (sam-sca)
tolvaptan
Tablets

Read the Medication Guide that comes with SAMSCA before you take it and each time you get a new prescription. There may be new information. This Medication Guide does not take the place of talking to your healthcare provider about your medical condition or your treatment. Share this important information with members of your household.

What is the most important information I should know about SAMSCA?

1) SAMSCA may make the salt (sodium) level in your blood rise too fast. This can increase your risk of a serious condition called osmotic demyelination syndrome (ODS). ODS can lead to coma or death. ODS can also cause new symptoms such as:

- trouble speaking
- swallowing trouble or feeling like food or liquid gets stuck while swallowing
- drowsiness
- confusion
- mood changes
- trouble controlling body movement (involuntary movement) and weakness in muscles of the arms and legs
- seizures

You or a family member should tell your healthcare provider right away if you have any of these symptoms even if they begin later in treatment. Also tell your healthcare provider about any other new symptoms while taking SAMSCA.

You may be more at risk for ODS if you have:

- liver disease
- not eaten enough for a long period of time (malnourished)
- very low sodium level in your blood
- been drinking large amounts of alcohol for a long period of time (chronic alcoholism)

To lessen your risk of ODS while taking SAMSCA:

- Treatment with SAMSCA should be started and re-started only in a hospital, where the sodium levels in your blood can be checked closely.
- Do not take SAMSCA if you cannot tell if you are thirsty.
- To prevent losing too much body water (dehydration), have water available to drink at all times while taking SAMSCA. Unless your healthcare provider tells you otherwise, drink when you are thirsty.
- If your healthcare provider tells you to keep taking SAMSCA after you leave a hospital, it is important that you do not stop and re-start SAMSCA on your own. You may need to go back to a hospital to re-start SAMSCA. Talk to your healthcare provider right away if you stop taking SAMSCA for any reason.
- It is important to stay under the care of your healthcare provider while taking SAMSCA and follow their instructions.

2) SAMSCA may cause liver problems, including life-threatening liver failure. SAMSCA should not be taken for more than 30 days. Tell your doctor right away if you develop or have worsening of any of these signs and symptoms of liver problems:

- Loss of appetite, nausea, vomiting
- Fever, feeling unwell, unusual tiredness
- Itching
- Yellowing of the skin or the whites of the eyes (jaundice)
- Unusual darkening of the urine
- Right upper stomach area pain or discomfort

3) If you have autosomal dominant polycystic kidney disease (ADPKD), do not use SAMSCA because you should receive the medicine (tolvaptan) through a program that ensures laboratory monitoring of your liver.

What is SAMSCA?

SAMSCA is a prescription medicine used to help increase low sodium levels in the blood, in adults with conditions such as heart failure, and certain hormone imbalances. SAMSCA helps raise salt levels in your blood by removing extra body water as urine.

It is not known if SAMSCA is safe or works in children.

Who should not take SAMSCA?

Do not take SAMSCA if:

- you are allergic to tolvaptan or any of the ingredients in SAMSCA. See the end of this Medication Guide for a complete list of ingredients in SAMSCA.
- the sodium level in your blood must be increased right away.
- you cannot replace fluids by drinking or you cannot feel if you are thirsty.
- you are dizzy, faint, or your kidneys are not working normally because you have lost too much body fluid.
- you take certain medicines. These medicines could cause you to have too much SAMSCA in your blood:
  - the antibiotic medicines, clarithromycin (Biaxin, Biaxin XL) or telithromycin (Ketek)
  - the antifungal medicines, ketoconazole (Nizoral) or itraconazole (Sporanox)
  - the anti-HIV medicines, ritonavir (Kaletra, Norvir), indinavir (Crixivan), nelfinavir (Viracept), and saquinavir (Invirase)
  - the antidepressant medicine, nefazodone hydrochloride
- your body is not able to make urine. SAMSCA will not help your condition.

What should I tell my healthcare provider before taking SAMSCA?

Tell your healthcare provider about all your medical conditions, including if you:

- have kidney problems and your body cannot make urine.
- have liver problems
- cannot feel if you are thirsty. See "What is the most important information I should know about SAMSCA?"
- had an allergic reaction in the past to tolvaptan or to any of the other ingredients of this medicine. See the end of this Medication Guide for a list of the ingredients in SAMSCA.
- are pregnant or plan to become pregnant. It is not known if SAMSCA will harm your unborn baby.
- are breast-feeding. It is not known if SAMSCA passes into your breast milk. You and your healthcare provider should decide if you will take SAMSCA or breast-feed. You should not do both.
- are taking desmopressin (dDAVP).

Tell your healthcare provider about all the medicines you take, including prescription and non-prescription medicines, vitamins, and herbal supplements.

Using SAMSCA with certain medicines could cause you to have too much SAMSCA in your blood. See "Who should not take SAMSCA?"

SAMSCA may affect the way other medicines work and other medicines may affect how SAMSCA works.

Know the medicines you take. Keep a list of them and show it to your healthcare provider and pharmacist when you get a new medicine.

How should I take SAMSCA?

- See "What is the most important information I should know about SAMSCA?"
- Take SAMSCA exactly as prescribed by your healthcare provider.
- Take SAMSCA one time each day.
- You can take SAMSCA with or without food.
- Do not drink grapefruit juice during treatment with SAMSCA. This could cause you to have too much SAMSCA in your blood.
- Certain medicines or illnesses may keep you from drinking fluids or may cause you to lose too much body fluid, such as vomiting or diarrhea. If you have these problems, call your healthcare provider right away.
- Do not miss or skip doses of SAMSCA. If you miss a dose, take it as soon as you remember. If it is near the time of the next dose, skip the missed dose. Just take the next dose at your regular time. Do not take 2 doses at the same time.
- If you take too much SAMSCA, call your healthcare provider right away. If you take an overdose of SAMSCA, you may need to go to a hospital.
- If your healthcare provider tells you to stop taking SAMSCA, follow their instructions about limiting the amount of fluid you should drink.

What are the possible side effects of SAMSCA?

SAMSCA can cause serious side effects including:

- See "What is the most important information I should know about SAMSCA?"
- Loss of too much body fluid (dehydration). Tell your healthcare provider if you:
  - have vomiting or diarrhea and cannot drink normally.
  - feel dizzy or faint. These may be symptoms that you have lost too much body fluid.

Call your healthcare provider right away if you have any of these symptoms.

The most common side effects of SAMSCA are:

- thirst
- dry mouth
- weakness
- constipation
- making large amounts of urine and urinating often
- increased blood sugar levels

These are not all the possible side effects of SAMSCA. Talk to your healthcare provider about any side effect that bothers you or that does not go away while taking SAMSCA.

Call your doctor for medical advice about side effects. You may report side effects to FDA at 1-800-FDA-1088.

How should I store SAMSCA?

Store SAMSCA between 59°F to 86°F (15°C to 30°C).

Keep SAMSCA and all medicines out of the reach of children.

General Information about SAMSCA

Medicines are sometimes prescribed for purposes other than those listed in a Medication Guide. Do not use SAMSCA for a condition for which it was not prescribed. Do not give SAMSCA to other people, even if they have the same symptoms you have. It may harm them.

This Medication Guide summarizes the most important information about SAMSCA. If you would like more information, talk with your healthcare provider. You can ask your healthcare provider or pharmacist for information about SAMSCA that is written for healthcare professionals. For more information about SAMSCA, call 1-877-726-7220 or go to www.samsca.com.

What are the ingredients in SAMSCA?

Active ingredient: tolvaptan.

Inactive ingredients: corn starch, hydroxypropyl cellulose, lactose monohydrate, low-substituted hydroxypropyl cellulose, magnesium stearate, microcrystalline cellulose, and FD&C Blue No. 2 Aluminum Lake as colorant.

Manufactured by Otsuka Pharmaceutical Co., Ltd., Tokyo, 101-8535 Japan

Distributed and marketed by Otsuka America Pharmaceutical, Inc., Rockville, MD 20850

SAMSCA is a registered trademark of Otsuka Pharmaceutical Co., Ltd., Tokyo, 101-8535 Japan

Rev. 4/2021

This Medication Guide has been approved by the U.S. Food and Drug Administration.

©2021 Otsuka Pharmaceutical Co., Ltd.

PRINCIPAL DISPLAY PANEL - 15 mg Tablet Blister Pack Carton

10 Tablets
NDC 59148-020-50

Carton contains 1 strip with 10 tablets.

Samsca®
(tolvaptan)
tablets

15 mg

MUST INITIATE IN HOSPITAL

DISPENSE THE ENCLOSED
MEDICATION GUIDE TO EACH PATIENT

Rx only

PRINCIPAL DISPLAY PANEL - 30 mg Tablet Blister Pack Carton

10 Tablets
NDC 59148-021-50

Carton contains 1 strip with 10 tablets.

Samsca®
(tolvaptan)
tablets

30 mg

MUST INITIATE IN HOSPITAL

DISPENSE THE ENCLOSED
MEDICATION GUIDE TO EACH PATIENT

Rx only